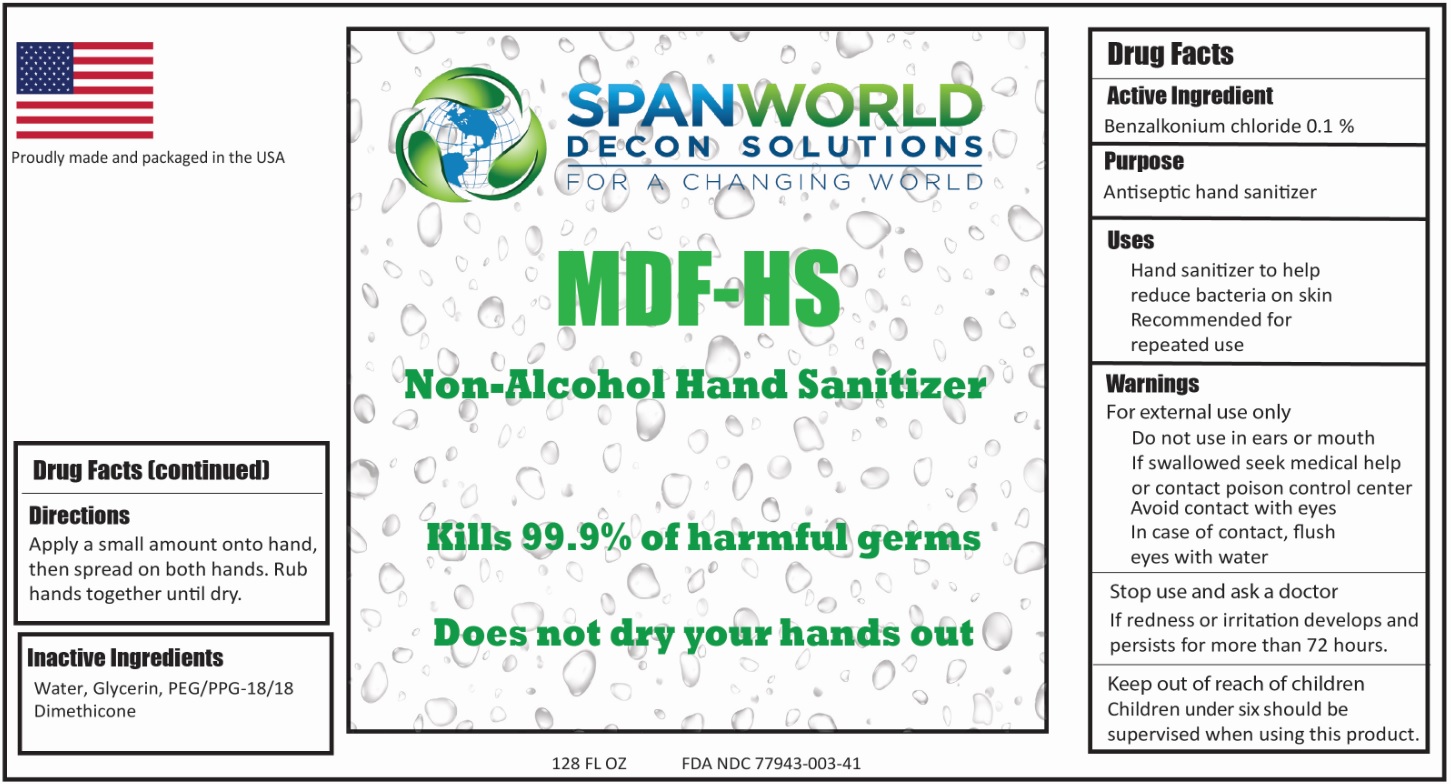 DRUG LABEL: MDF-HS
NDC: 77943-003 | Form: LIQUID
Manufacturer: Span-World LLC
Category: otc | Type: HUMAN OTC DRUG LABEL
Date: 20201201

ACTIVE INGREDIENTS: BENZALKONIUM CHLORIDE 1.05 g/100 g
INACTIVE INGREDIENTS: PEG/PPG-18/18 DIMETHICONE 0.5 g/100 g; GLYCERIN 0.5 g/100 g; WATER 96.95 g/100 g

MDF HS Non-Alcohol Topical Hand Sanitizer